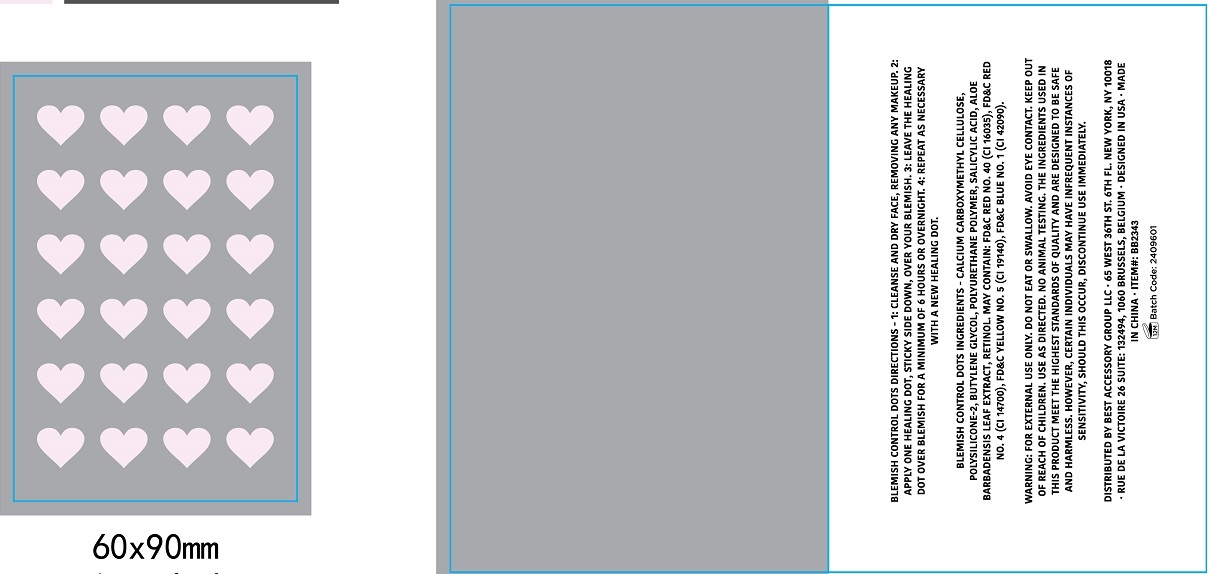 DRUG LABEL: Blemish Control Dots
NDC: 56136-184 | Form: PATCH
Manufacturer: Ganzhou Olivee Cosmetic Co., Ltd.
Category: otc | Type: HUMAN OTC DRUG LABEL
Date: 20240320

ACTIVE INGREDIENTS: SALICYLIC ACID 0.5 g/100 g
INACTIVE INGREDIENTS: MELALEUCA ALTERNIFOLIA (TEA TREE) LEAF OIL; BUTYLENE GLYCOL; CARBOXYMETHYLCELLULOSE CALCIUM; ASCORBIC ACID; ROSA CANINA FRUIT OIL; FD&C RED NO. 40; FD&C RED NO. 4; FD&C YELLOW NO. 5; FD&C BLUE NO. 1

24 patches blemish control dots

Active Ingredients

Salicylic Acid 0.5%

Purpose

Acne Treatment

Uses

soothe and helps diminish the redness and irritation of blemished skin and absorbs excess oil for faster healing.

Directions

- Cleanse and dry facem, removing and makeup.
- Apply one healing dot, sticky side down, over your blemish.
- Leave the healing dot over blemish for at least 6 hours or overnight
- Repeat as necessary with a new healing dot.

Inactive Ingredients

Calcium Carboxymethyl Cellulose, polysilicone-2, Butylene Glycol. Polyurethan polymer, Melaleuca Alternifolia (Tea Tree) Leaf Oil, May contain: FD&C Red No. 40 (CI 16035) FD&C RED NO. 4 (CI14700), FD&C YELLOW NO. 5 (CI19140),FD&C BLUE NO.1 (CI42090)

Warnings

For external use only.

When using this product

- skin irritation and dryness is more likely to occur if you use another topical acne medication at the same time. If irritation occurs, only use one topical acne medication at a time.
- The ingredients used in this product meet the highest standards of quality and are infrequent instances of sensitivity, sould this occur, discontinue use immediately.

Keep out of reach of children. If swallowed, get medical help or contact a Poison Control center right away